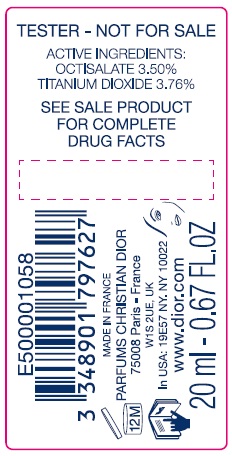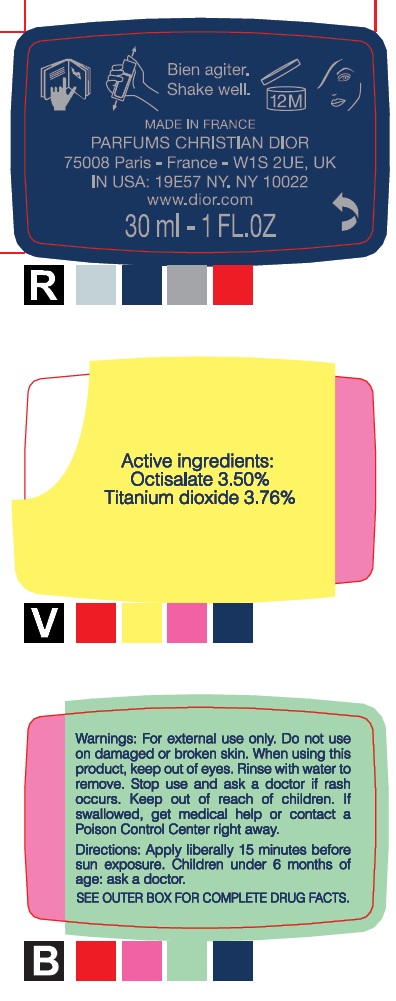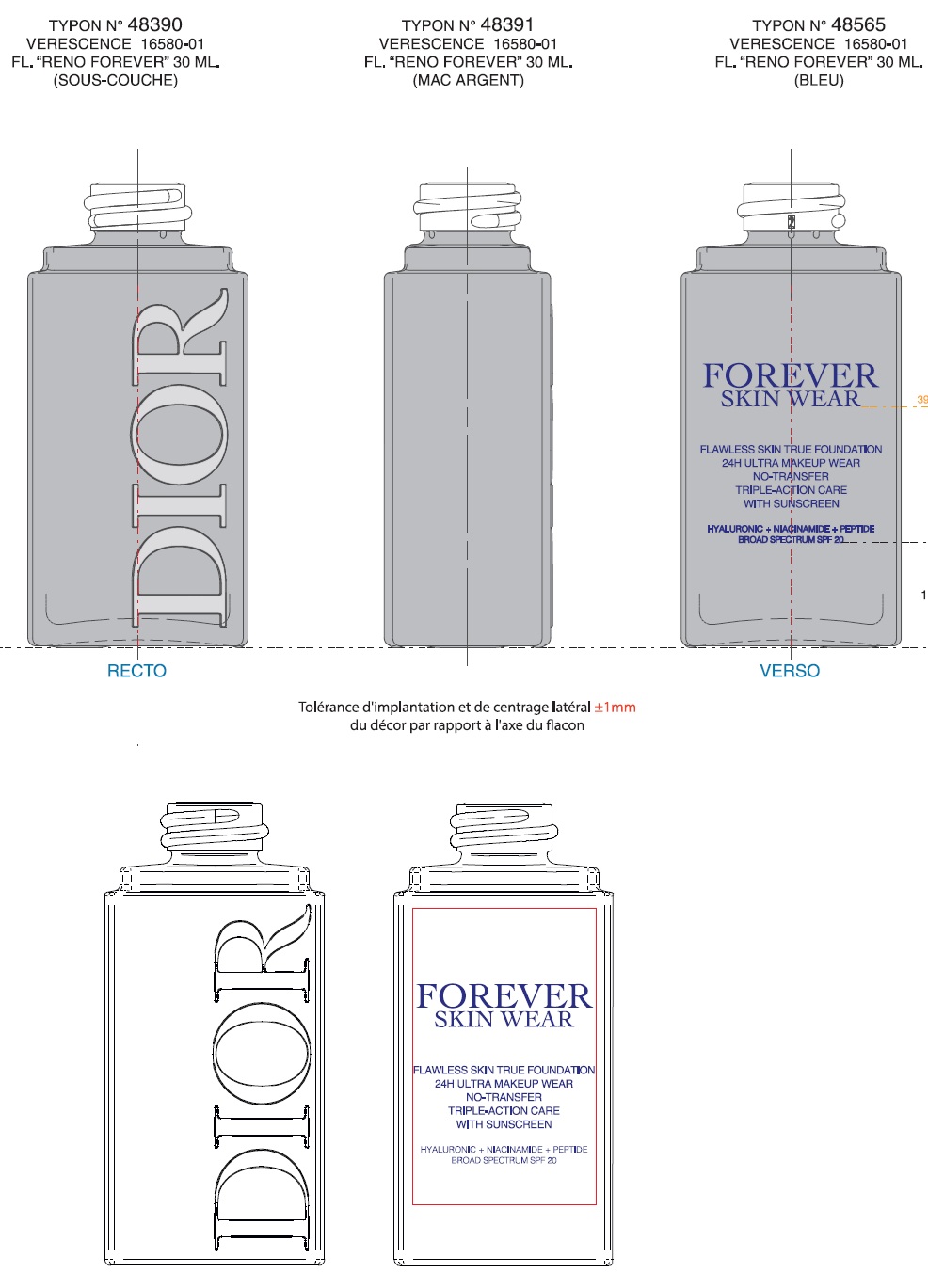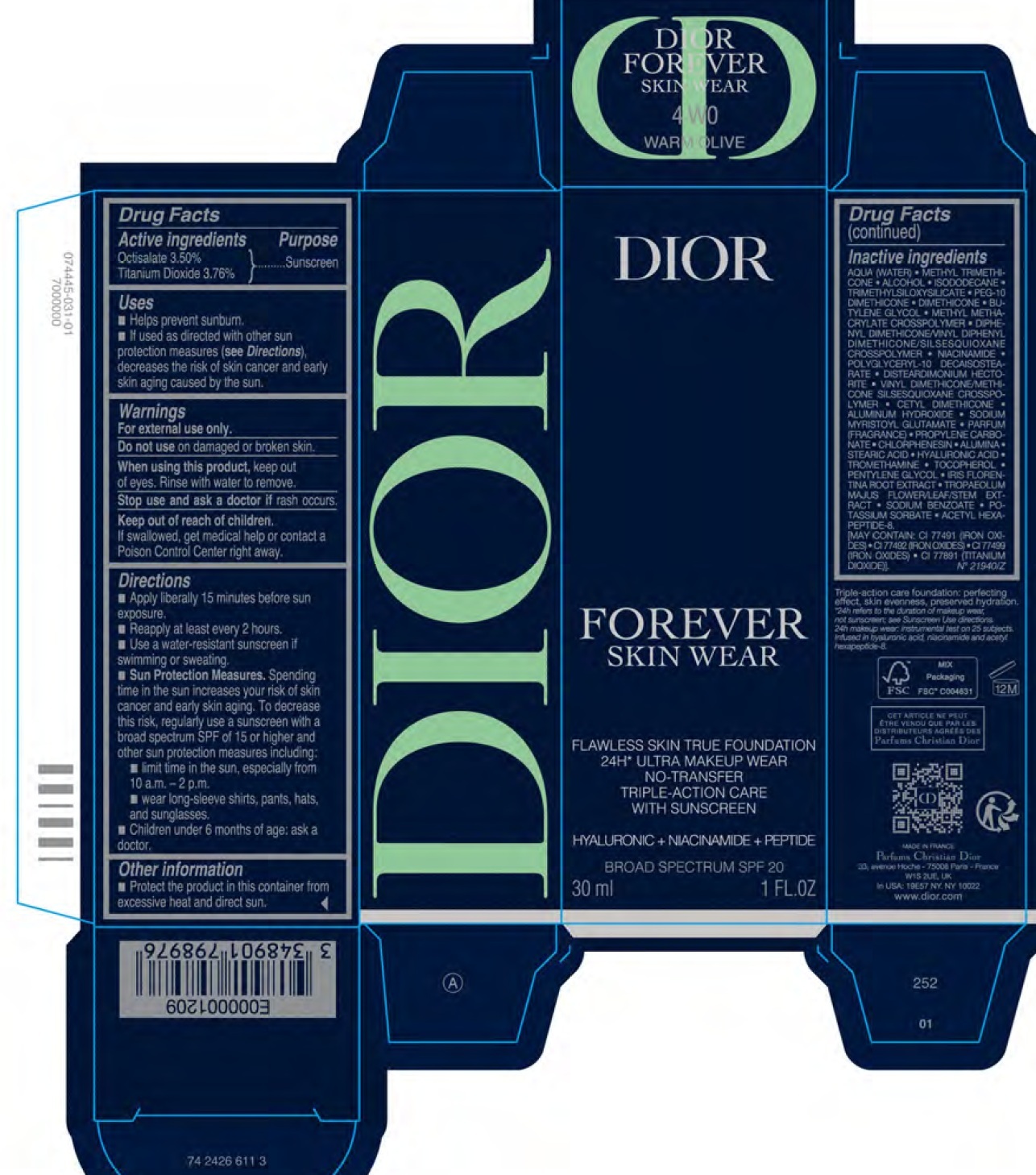 DRUG LABEL: Dior Forever Skin Wear Flawless Skin True Foundation SPF 20 4WO Warm Olive
NDC: 61957-3431 | Form: EMULSION
Manufacturer: Parfums Christian Dior
Category: otc | Type: HUMAN OTC DRUG LABEL
Date: 20260116

ACTIVE INGREDIENTS: OCTISALATE 35 mg/1 mL; TITANIUM DIOXIDE 37.6 mg/1 mL
INACTIVE INGREDIENTS: WATER; METHYL TRIMETHICONE; ALCOHOL; ISODODECANE; DIMETHICONE; BUTYLENE GLYCOL; NIACINAMIDE; POLYGLYCERYL-10 DECAISOSTEARATE; DISTEARDIMONIUM HECTORITE; VINYL DIMETHICONE/METHICONE SILSESQUIOXANE CROSSPOLYMER; ALUMINUM HYDROXIDE; SODIUM MYRISTOYL GLUTAMATE; PROPYLENE CARBONATE; CHLORPHENESIN; ALUMINUM OXIDE; STEARIC ACID; HYALURONIC ACID; TROMETHAMINE; TOCOPHEROL; PENTYLENE GLYCOL; IRIS X GERMANICA NOTHOVAR. FLORENTINA ROOT; TROPAEOLUM MAJUS FLOWERING TOP; SODIUM BENZOATE; POTASSIUM SORBATE; ACETYL HEXAPEPTIDE-8 AMIDE

Dior Forever Skin Wear Flawless Skin True Foundation SPF 20 4WO Warm Olive

Active ingredients

Octisalate 3.50%

Titanium Dioxide 3.76%

Purpose

Sunscreen

Uses

- Helps prevent sunburn.
- If used as directed with other sun protection measures (see Directions), decreases the risk of skin cancer and early skin aging caused by the sun.

Warnings

For external use only.

Do not use

on damaged or broken skin.

When using this product,

keep out of eyes. Rinse with water to remove.

Stop use and ask a doctor if

rash occurs.

Keep out of reach of children.

If swallowed, get medical help or contact a Poison Control Center right away.

Directions

- Apply liberally 15 minutes before sun exposure.
- Reapply at least every 2 hours.
- Use a water-resistant sunscreen if swimming or sweating.
- Sun Protection Measures.Spending time in the sun increases your risk of skin cancer and early skin aging. To decrease this risk, regularly use a sunscreen with a broad spectrum SPF of 15 or higher and other sun protection measures including:
- limit time in the sun, especially from 10 a.m. - 2 p.m.
- wear long-sleeve shirts, pants, hats, and sunglasses.
- Children under 6 months of age: ask a doctor.

Other information

- Protect the product in this container from excessive heat and direct sun.

Inactive ingredients

AQUA (WATER) • METHYL TRIMETHICONE • ALCOHOL • ISODODECANE • TRIMETHYLSILOXYSILICATE • PEG-10 DIMETHICONE • DIMETHICONE • BUTYLENE GLYCOL • METHYL METHACRYLATE CROSSPOLYMER • DIPHENYL DIMETHICONE/VINYL DIPHENYL DIMETHICONE/SILSESQUIOXANE CROSSPOLYMER • NIACINAMIDE • POLYGLYCERYL-10 DECAISOSTEARATE • DISTEARDIMONIUM HECTORITE • VINYL DIMETHICONE/METHICONE SILSESQUIOXANE CROSSPOLYMER • CETYL DIMETHICONE • ALUMINUM HYDROXIDE • SODIUM MYRISTOYL GLUTAMATE • PARFUM (FRAGRANCE) • PROPYLENE CARBONATE • CHLORPHENESIN • ALUMINA • STEARIC ACID • HYALURONIC ACID • TROMETHAMINE • TOCOPHEROL • PENTYLENE GLYCOL • IRIS FLORENTINA ROOT EXTRACT • TROPAEOLUM MAJUS FLOWER/LEAF/STEM EXTRACT • SODIUM BENZOATE • POTASSIUM SORBATE • ACETYL HEXAPEPTIDE-8
[MAY CONTAIN : CI 77491 (IRON OXIDES), CI 77492 (IRON OXIDES) , CI 77499 (IRON OXIDES), CI 77891 (TITANIUM DIOXIDE)]. N° 21940/Z